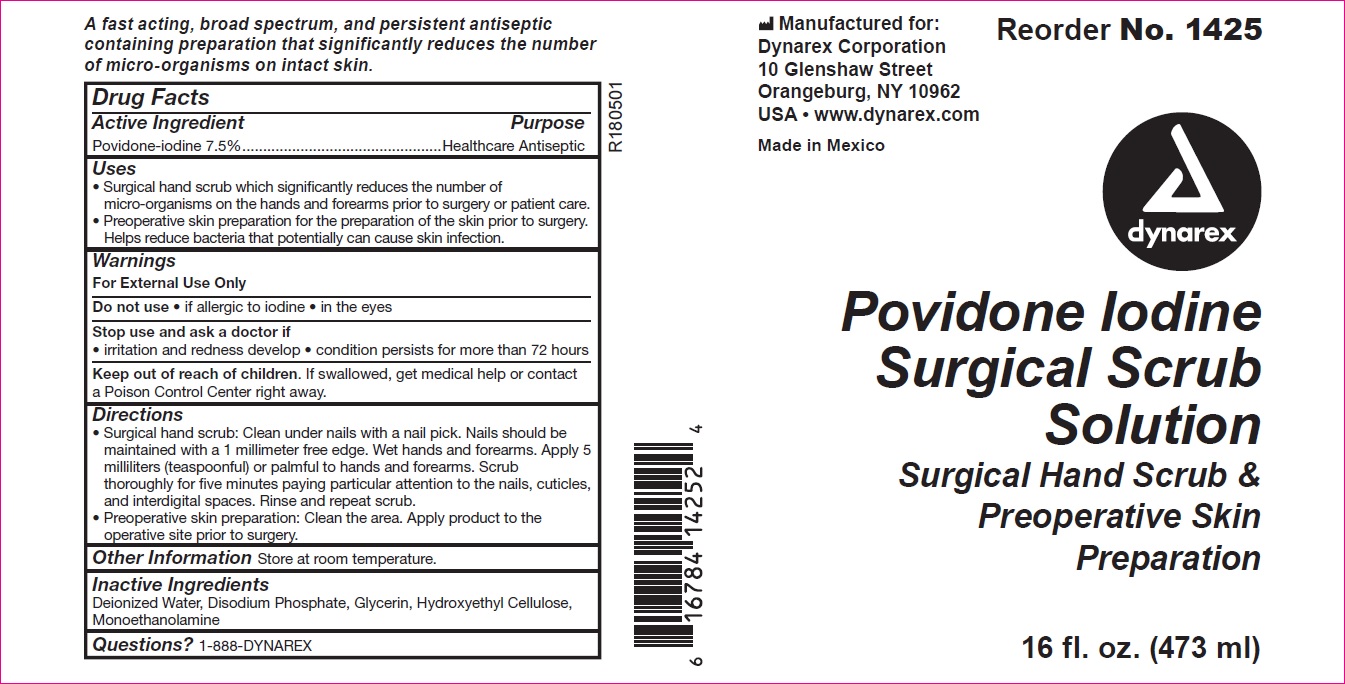 DRUG LABEL: Dynarex Povidone Iodine Surgical Scrub
NDC: 67777-142 | Form: LIQUID
Manufacturer: Dynarex Corporation
Category: otc | Type: HUMAN OTC DRUG LABEL
Date: 20241120

ACTIVE INGREDIENTS: POVIDONE-IODINE 100 mg/7.5 mL
INACTIVE INGREDIENTS: WATER; SODIUM PHOSPHATE, DIBASIC, ANHYDROUS; HYDROXYETHYL CELLULOSE (100 MPA.S AT 2%); MONOETHANOLAMINE; GLYCERIN

1425, 1426

Active Ingredient

Povidone-iodine 7.5%

Purpose

Healthcare Antiseptic

Uses

- Surgical hand scrub which significantly reduces the number of micro-organisms on the hands and forearms prior to surgery or patient care.
- Preoperative skin preparation for the preparation of the skin prior to surgery. Helps reduce bacteria that potentially can cause skin infection

Warnings

For external use only

Do Not Use

- if allergic to iodine
- in the eyes

Stop use and ask a doctor if

- irritation and redness develop
- condition persists for more than 72 hours

Keep out of reach of children. If swallowed, get medical help or contact a Poison Control Center right away.

Directions

- Surgical hand scrub: Clean under nails with a nail pick. Nails should be maintained with a 1 millimeter free edge. Wet hands and forearms. Apply 5 milliliters (teaspoonful) or palmful to hands and forearms. Scrub thoroughly for five minutes paying particular attention to the nails, cuticles, and interdigital spaces. Rinse and repeat scrub.
- Preoperative skin preparation: Clean the area. Apply product to the operative site prior to surgery.

Other

Store at controlled room temperature.

Inactive Ingredients

Citric Acid, Disodium Phosphate, Glycerin, Puried Water, Sodium Citrate, Tween 80

Questions?

1-888-DYNAREX